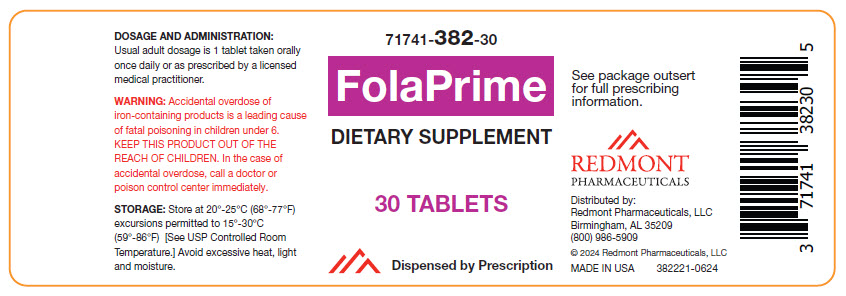 DRUG LABEL: FolaPrime
NDC: 71741-382 | Form: TABLET
Manufacturer: Redmont Pharmaceuticals, LLC
Category: other | Type: DIETARY SUPPLEMENT
Date: 20240715

ACTIVE INGREDIENTS: BETA CAROTENE 300 ug/1 1; Ascorbic Acid 60 mg/1 1; Cholecalciferol 10 ug/1 1; .ALPHA.-TOCOPHEROL ACETATE 4.5 mg/1 1; PYRIDOXINE HYDROCHLORIDE 26 mg/1 1; Biotin 0.28 mg/1 1; Folic Acid 0.4 mg/1 1; LEVOMEFOLATE CALCIUM 0.6 mg/1 1; Cyanocobalamin 0.013 mg/1 1; Calcium Carbonate 80 mg/1 1; Magnesium Oxide 25 mg/1 1; FERROUS BISGLYCINATE 20 mg/1 1; Potassium Iodide 0.15 mg/1 1
INACTIVE INGREDIENTS: MICROCRYSTALLINE CELLULOSE 102; Maltodextrin; Croscarmellose Sodium; Silicon Dioxide; Stearic Acid; MAGNESIUM PALMITOSTEARATE; HYPROMELLOSE, UNSPECIFIED; POLYETHYLENE GLYCOL, UNSPECIFIED; Titanium Dioxide; FD&C Blue No. 1

FolaPrime

STATEMENT OF IDENTITY

FolaPrime 71741-382-30
Multivitamin Dietary Supplement
Dispensed by Prescription

DESCRIPTION

FolaPrime is a prescription multivitamin/multimineral dietary supplement.

STATEMENT OF IDENTITY

Supplement Facts
Serving size 1 Tablet
Amount per Serving: | %Daily Value
Vitamin A (as Beta-Carotene) | 300 mcg RAE | 33%
Vitamin C (as Ascorbic Acid) | 60 mg | 67%
Vitamin D (as Cholecalciferol) | 10 mcg | 50%
Vitamin E (as dl-Alpha Tocopherol Acetate) | 4.5 mg (10 IU) | 33%
Vitamin B6 (as Pyridoxine HCl) | 26 mg | 1529%
Biotin | 0.280 mg | 933%
Folate | 1.67 mg DFE | 418%
(from Folic Acid) | 0.67 mg DFE | [Daily Value not established]
(from 5-Methyl Tetrahydrofolate, Calcium Salt) | 1 mg DFE
Vitamin B12 (as Cyanocobalamin) | 0.013 mg | 542%
Calcium (as Calcium Carbonate) | 80 mg | 6%
Magnesium (as Magnesium Oxide) | 25 mg | 6%
Ferrochel™ Iron (as Ferrous BisGlycinate Chelate) | 20 mg | 111%
Iodine (as Potassium Iodide) | 0.150 mg | 100%

OTHER INGREDIENTS: Microcrystalline Cellulose, Maltodextrin, Croscarmellose Sodium, Silicon Dioxide, Stearic Acid, Magnesium Stearate, Film Coating (Hydroxypropyl Methylcellulose, Polyethylene Glycol, Titanium Dioxide, FD&C Blue # 1)

Allergen: NONE

INDICATIONS

FolaPrime is a prescription multivitamin/multimineral dietary supplement formulated for the clinical dietary management of suboptimal nutritional status in patients where advanced folate, vitamin B supplementation, and maintenance of good health is needed.

CONTRAINDICATIONS

FolaPrime is contraindicated in patients with a known hypersensitivity to any of the ingredients.

PRECAUTIONS

Folic acid alone is improper therapy in the treatment of pernicious anemia and other megaloblastic anemias where Vitamin B12 is deficient. Folic acid in doses above 1.0 mg daily may obscure pernicious anemia in that hematologic remission can occur while neurological manifestations progress.

WARNINGS

WARNING: Accidental overdose of iron-containing products is a leading cause of fatal poising in children under 6. Keep this product out of the reach of children. In the case of accidental overdose, call a doctor or poison control center immediately.

ADVERSE REACTIONS

Allergic sensitization has been reported following both oral and parenteral administration of folic acid.

You should call your doctor for medical advice about serious adverse events. To report adverse side effects or to obtain product information, contact Redmont Pharmaceuticals, LLC at 1-800-986-5909.

DOSAGE AND ADMINISTRATION

One tablet daily or as directed by a physician.

HOW SUPPLIED

Bottles of 30 tablets (71741-382-30 [Redmont Pharmaceuticals does not represent this product code to be National Drug Code (NDC). Product codes are formatted according to standard industry practice, to meet the formatting requirement by pedigree reporting and supply-chain control including pharmacies.]). Tablet is blue, oblong.

This product is a prescription-folate with or without other dietary ingredients that – due to increased folate levels increased risk associated with masking B12 deficiency (pernicious anemia) requires administration under the care of a licensed medical practitioner (64 FR 8760). 1-3 The most appropriate way to ensure pedigree reporting consistent with these regulatory guidelines and safety monitoring is to dispense this product only by prescription. This is not an Orange Book product. This product may be administered only under a physician's supervision and all prescriptions using this product shall be pursuant to state statues as applicable. The ingredients, indication or claims of this product are not to be construed to be drug claims.

1. Federal Register Notice of August 2, 1973 (38 FR 20750)
2. Federal Register Notice of October 17, 1980 (45 FR 69043, 69044)
3. Federal Register Notice of March 5, 1996 (61 FR 8760)

STORAGE AND HANDLING

STORAGE

Store at 20°-25° C (68°-77°F) excursions permitted to 15°-30°C (59°-86°F) [See USP Controlled Room Temperature.] Avoid excessive heat, light and moisture.

TAMPER EVIDENT: Do not use if seal is broken or missing.

HEALTH CLAIM

MADE IN USA

Distributed by:

Redmont Pharmaceuticals, LLC
Birmingham, AL 35209
800-986-5909

Ferrochel™ is a trademark of Albion Laboratories, Inc.

These statements have not been evaluated by the Food and Drug Administration. This product is not intended to diagnose, treat, cure, or prevent any disease.

SAFE HANDLING WARNING

KEEP THIS AND ALL MEDICATIONS OUT OF THE REACH OF CHILDREN

HEALTH CLAIM

© 2024 Redmont Pharmaceuticals, LLC
382111-0624

PRINCIPAL DISPLAY PANEL - 30 Tablet Bottle Label

71741-382-30

FolaPrime
DIETARY SUPPLEMENT

30 TABLETS

Dispensed by Prescription